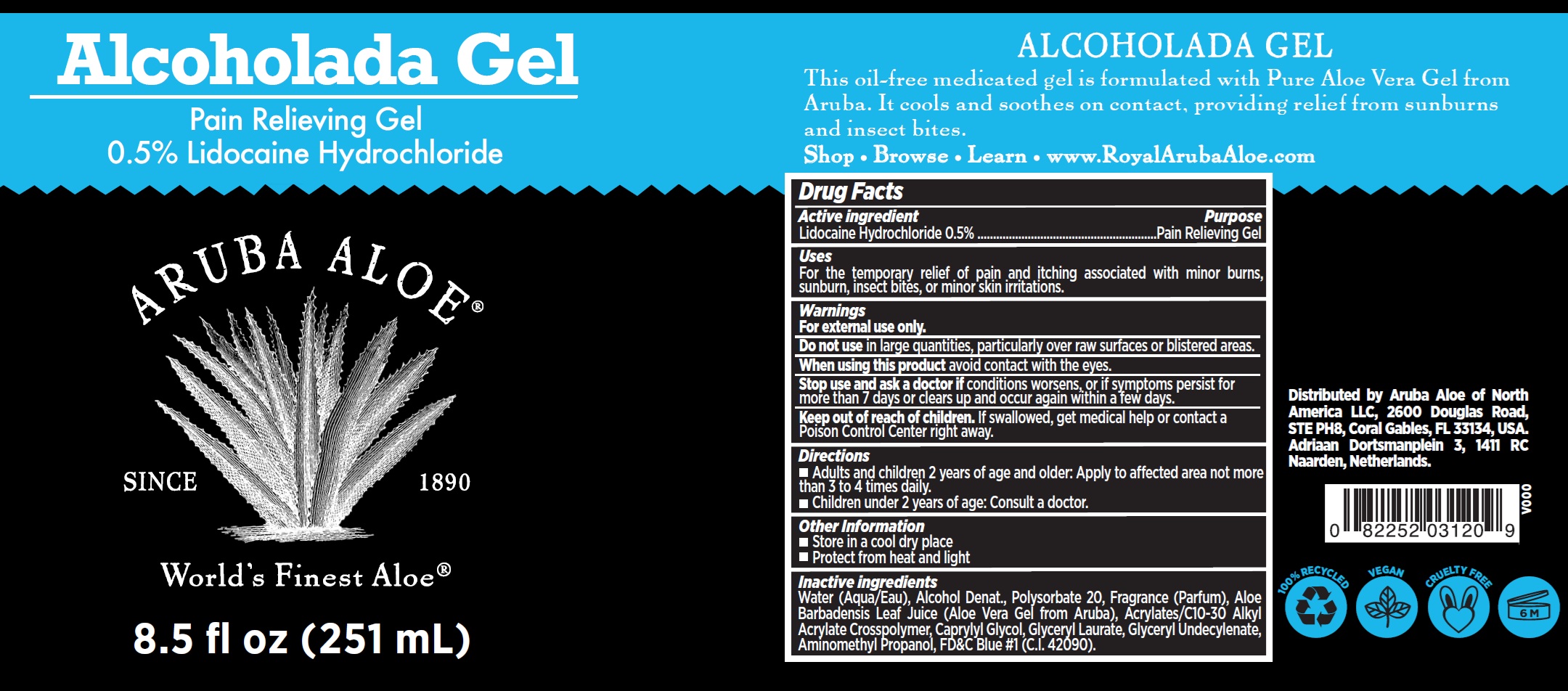 DRUG LABEL: Aruba Aloe Alcoholada
NDC: 53675-212 | Form: CREAM
Manufacturer: Aruba Aloe Balm NV
Category: otc | Type: HUMAN OTC DRUG LABEL
Date: 20250807

ACTIVE INGREDIENTS: LIDOCAINE HYDROCHLORIDE 5 mg/1 mL
INACTIVE INGREDIENTS: WATER; ALCOHOL; POLYSORBATE 20; ALOE VERA LEAF; CAPRYLYL GLYCOL; GLYCERYL LAURATE; AMINOMETHYLPROPANOL; FD&C BLUE NO. 1

Aruba Aloe Alcoholada Gel

Active ingredient

Lidocaine Hydrochloride 0.5%

Purpose

Pain Relieving Gel

Uses

For the temporary relief of pain and itching associated with minor burns, sunburn, insect bites, or minor skin irritations.

Warnings

For external use only.

Do not use

in large quantities, particularly over raw surfaces or blistered areas.

When using this product

avoid contact with the eyes.

Stop use and ask a doctor if

conditions worsens, or if symptoms persist for more than 7 days or clears up and occur again within a few days.

Keep out of reach of children.

If swallowed, get medical help or contact a Poison Control Center right away.

Directions

- Adults and children 2 years of age and older: Apply to affected area not more than 3 to 4 times daily.
- Children under 2 years of age: Consult a doctor.

Other Information

- Store in a cool dry place
- Protect from heat and light

Inactive Ingredients

Water (Aqua/Eau), Alcohol Denat., Polysorbate 20, Fragrance (Parfum), Aloe Barbadensis Leaf Juice (Aloe Vera Gel from Aruba), Acrylates/C10-30 Alkyl Acrylate Crosspolymer, Caprylyl Glycol, Glyceryl Laurate, Glyceryl Undecylenate, 8.5 fl oz (251 mL) Aminomethyl Propanol, FD&C Blue #1 (C.I. 42090).